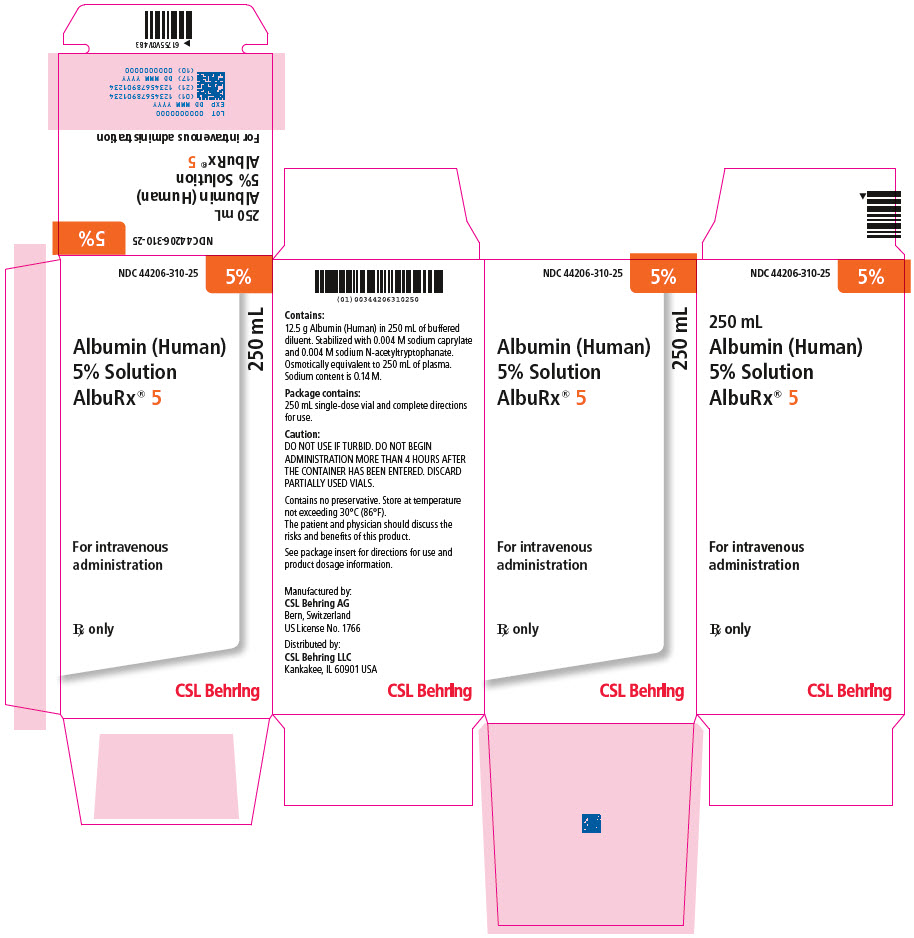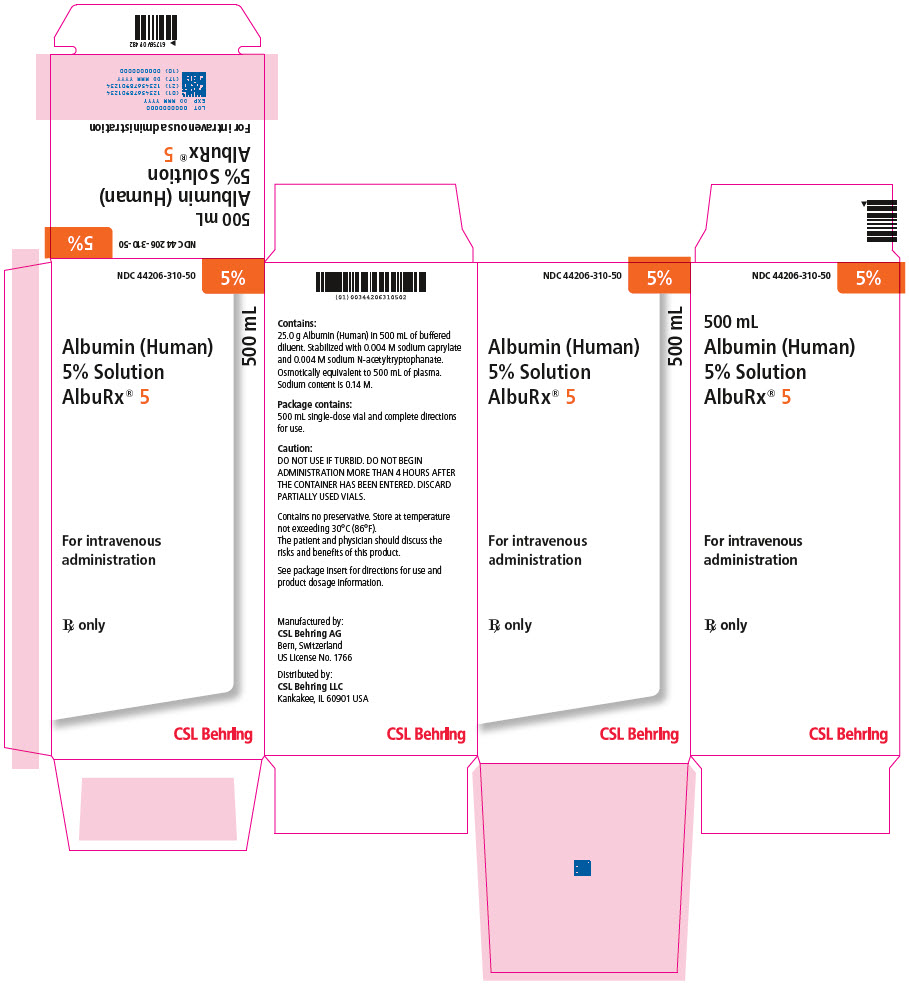 DRUG LABEL: ALBURX
NDC: 44206-310 | Form: SOLUTION
Manufacturer: CSL Behring AG
Category: other | Type: PLASMA DERIVATIVE
Date: 20220804

ACTIVE INGREDIENTS: ALBUMIN HUMAN 12.5 g/250 mL
INACTIVE INGREDIENTS: SODIUM CHLORIDE; POTASSIUM CHLORIDE; N-ACETYL-DL-TRYPTOPHAN SODIUM; SODIUM CAPRYLATE

Albumin (Human) 5% Solution
ALBURX® 5

RX only

DESCRIPTION

ALBURX® 5, Albumin (Human) 5% solution is a sterile aqueous solution for intravenous administration containing the albumin component of human blood. The solution is clear and slightly viscous; it is almost colorless, or yellow, amber, or green.

This product is prepared from the plasma of US donors. The product has been produced by alcohol fractionation and has been heated for 10 hours at 60°C for inactivation of infectious agents. The results of virus validation studies have shown that the manufacturing process, particularly alcohol fractionation, eliminates enveloped and non-enveloped viruses. Additionally, heat treatment at 60°C for a period of 10 hours efficiently inactivates viruses. The solution contains 0.14 M (3.2 mg/mL) sodium. The aluminum content is ≤ 200 mcg/L and the potassium content is ≤ 0.002 M. The solution is stabilized with 0.004 M sodium N-acetyltryptophanate and 0.004 M sodium caprylate. The solution contains no preservative.

CLINICAL PHARMACOLOGY^10,16

ALBURX® 5, Albumin (Human) 5% solution should not be used as an intravenous nutrient because of the slow breakdown and relatively unfavorable composition of the albumin molecule with respect to its content of essential amino acids. Oral provision of proteins or an intravenous regimen providing adequate calories and a suitable amino acid mixture are the methods of choice for the treatment of protein malnutrition as such, though they do not permit the rapid correction of hypoproteinemia.

The binding properties of albumin may, in special circumstances, provide an indication for its clinical use. For such purposes, however, an Albumin (Human) 25% solution should be used.

The colloid osmotic or oncotic properties of albumin constitute the predominant reason for its clinical use. The rationale for this is the Starling concept of the capillary balance of hydrostatic and oncotic pressure gradients across the capillary walls as the determinant of the fluid – i.e. volume – distribution between the intravascular and the interstitial compartment.^15 The basic indication for the use of ALBURX® 5, Albumin (Human) 5% solution is therefore a plasma or blood volume deficit. The 5% concentration is approximately isotonic and isooncotic with normal human plasma. The effective colloid osmotic pressure of the serum proteins depends very largely on the relatively small and numerous albumin molecules, which therefore play a decisive role in the maintenance of the circulating plasma volume.

INDICATIONS AND USAGE

Shock

The definitive treatment of major hemorrhage is the transfusion of red blood cells restoring a normal oxygen transport capacity of the blood. Since, however, the life-threatening event in major hemorrhage is the loss of blood volume and not the erythrocyte deficit, the blood volume can, as an emergency measure, be supported by ALBURX® 5, Albumin (Human) 5% solution or another rapidly acting plasma substitute if blood is not immediately available. This will restore cardiac output and abolish circulatory failure with tissue anoxia. Though a four- to fivefold volume of crystalloids may be equally effective, their administration takes more time and creates a general overload with sodium and water. In the presence of dehydration, electrolyte solutions such as Ringer's lactate should be administered in conjunction with albumin.

Burns

Apart from damage to the respiratory tract, the development of burn shock is the most life-threatening event in the immediate care of the burned patient. Therapy during the first 24 hours is directed at the administration of large volumes of crystalloid solutions and lesser amounts of ALBURX® 5, Albumin (Human) 5% solution to maintain an adequate plasma volume and protein (colloid) content. For continuation of therapy beyond 24 hours, larger amounts of ALBURX® 5, Albumin (Human) 5% solution and lesser amounts of crystalloid are generally used.^16 An optimum regimen for the use of Albumin (Human), electrolytes, and fluid in the early treatment of burns has, however, not yet been established.

Pancreatitis and peritonitis

ALBURX® 5, Albumin (Human) 5% solution is useful in the early therapy of shock associated with acute hemorrhagic pancreatitis and peritonitis. It has been found that the correction of the blood volume deficit and adequate fluid therapy are mandatory in the acute stage of pancreatitis and peritonitis when there is loss of fluid into the peritoneal cavity or the retroperitoneal space.^1

Postoperative albumin loss

It is now recognized that intra-operative damage to capillary walls by blunt handling and sharp dissection of tissues leads to substantial postoperative losses of circulating albumin, over and above those due to bleeding. Forty to eighty percent of the intravascular albumin mass may thus be lost after radical dissections for malignant disease, surgery of the colon and rectum, and reconstructive procedures involving the aorta and major iliac vessels.^4,7,14 ALBURX® 5, Albumin (Human) 5% solution is a suitable agent for the correction of the resultant loss of plasma volume and in this situation may be superior to electrolyte solutions in maintaining early postoperative pulmonary function.^13 However, temporary redistribution of protein is usually not an indication for Albumin (Human).

Hypoproteinemia with an oncotic deficit

In subacute or chronic hypoproteinemia, efforts should always be made to determine the underlying cause and to improve circulating protein levels by dietary means. Most commonly, such states are due to protein-calorie malnutrition, defective absorption in gastrointestinal disorders, faulty albumin synthesis in chronic hepatic failure, increased protein catabolism postoperatively or with sepsis, and abnormal renal losses of albumin with chronic kidney disease. In all these situations, the circulating plasma volume is usually maintained by the renal retention of sodium and water, but this is associated with tissue edema due to the hypoalbuminemia with an oncotic deficit. The cutaneous edema lowers the oxygen tension of wounds and may thus impair the healing process^3, and the oncotic deficit favors the development of interstitial pulmonary edema^2 and the intestinal accumulation of fluids, which may progress to a paralytic ileus.^7 Though relief of the basic pathology is the definitive mode of therapy for the restoration of the plasma protein content, this process takes time to become effective, and the rapid correction of an oncotic deficit by the administration of Albumin (Human) may be indicated. For this purpose, however, Albumin (Human) 25% is preferable, possibly in conjunction with a diuretic.^12 It is emphasized that whereas Albumin (Human) may be needed to treat the aforementioned acute complications of chronic hypoproteinemia, it is not indicated for treatment of the chronic condition itself.

CONTRAINDICATIONS

The use of ALBURX® 5, Albumin (Human) 5% solution is contraindicated in patients with a history of an incompatibility reaction to such preparations (see ADVERSE REACTIONS). In addition, ALBURX® 5 may be contraindicated in patients with cardiac failure or severe anemia because of the risk of acute circulatory overload.

WARNINGS

ALBURX® 5, Albumin (Human) 5% solution is made from human plasma. Products made from human plasma may contain infectious agents, such as viruses, that can cause disease. The risk that such products will transmit an infectious agent has been extremely reduced by screening plasma donors for prior exposure to certain viruses, by testing for the presence of certain current virus infections, and by inactivating and/or removing certain viruses through alcohol fractionation and through heat treatment of the product in the final container for 10 hours at 60ºC. Despite these measures, such products can still potentially transmit disease. A theoretical risk for transmission of Creutzfeldt-Jakob Disease (CJD) is considered extremely remote. No cases of transmission of viral diseases or CJD have ever been identified for Albumin (Human). There is also the possibility that unknown infectious agents may be present in such products. All infections thought by a physician possibly to have been transmitted by this product should be reported by the physician or other healthcare provider to CSL Behring Pharmacovigilance Department at 1-866-915-6958.

The physician should discuss the risks and benefits of this product with the patient.

Turbid solutions must not be used. Do not begin administration more than 4 hours after introduction of the administration set.

PRECAUTIONS

Adequate precautions should be taken against circulatory overload (see DOSAGE AND ADMINISTRATION). Acute pulmonary edema is seen in 3 to 4 percent of patients resuscitated from severe shock, but this is neither related to any particular type of resuscitative fluid, nor is it necessarily due to circulatory overload.^11 Helpful measures are pulmonary auscultation and if possible measurement of the central venous pressure. Special caution is indicated in patients with stabilized chronic anemia or renal insufficiency.

PREGNANCY

Animal reproduction studies have not been conducted with ALBURX® 5, Albumin (Human) 5% solution. It is also not known whether ALBURX® 5 can cause fetal harm when administered to a pregnant woman or can affect reproduction capacity. ALBURX® 5 should be given to a pregnant woman only if clearly needed. There is, however, no evidence for any contraindication to the use of ALBURX® 5 specifically associated with reproduction, pregnancy or the fetus.

Use an intravenous infusion set suitable for the infusion of blood and blood products.

ADVERSE REACTIONS

Since ALBURX® 5, Albumin (Human) 5% solution is sterile when coming from the manufacturer, bacterial contamination with the risk of post-infusion septicemia can only occur if the container has been damaged or following puncture of the rubber cap (see WARNINGS).

Though very rare, non-septic incompatibility reactions including nausea, chills, fever, urticaria, headache and hypotension following the administration of albumin-containing preparations have occasionally been observed.^6,8,9,16 A favorable response to the intravenous administration of 50 to 100 mg of prednisolone was recorded.^9 Severe allergic reactions such as anaphylactic shock have been reported.

DOSAGE AND ADMINISTRATION

ALBURX® 5, Albumin (Human) 5% solution must be administered intravenously. The venipuncture site should not be infected or traumatized, and should be prepared with standard aseptic technique. The solution is compatible with whole blood or packed red cells as well as the usual electrolyte and carbohydrate solutions intended for intravenous use. By contrast, it should not be mixed with protein hydrolysates, amino acid mixtures, or solutions containing alcohol. It is ready for use as contained in the bottle and may be given without regard to the blood group of the recipient.

Upon administration of ALBURX® 5, Albumin (Human) 5% solution, there is a rapid increase of the plasma volume about equal to the volume infused. The initial dose for adults is 250 or 500 mL. The rate of infusion and the total volume administered are determined by the condition and response of the patient. A rate of 1–2 mL per minute is usually suitable in the absence of overt shock, whereas the capacity of the administration set is the only limit in the exsanguinated patient.

During resuscitation, constant monitoring of the patient provides the guidelines for treatment.

For children, a dose of 22 to 33 mL per kilogram body weight is usually adequate and close surveillance of the young patient is essential. Since patients – notably those with sepsis or severe multiple injuries – often need a circulating blood volume exceeding the prediction derived from their body weight, treatment should always be guided by the hemodynamic response and not by blood volume calculations or measurements.^5

ALBURX® 5, Albumin (Human) 5% is clear and slightly viscous; it is almost colorless, or yellow, amber, or green. Parenteral drug products should be inspected visually for particulate matter and discoloration prior to administration, whenever solution and container permit. Do not use solution that is turbid or contains particulate matter. Partially used bottles must be discarded.

HOW SUPPLIED

ALBURX® 5 is supplied as a 5% solution (50 g/L).

Each product presentation includes a package insert and the following components listed in Table 1 below.

Table 1. How Supplied
Presentation | Carton NDC Number | Components
250 mL | 44206-310-25 | One single-dose vial containing 12.5 grams of albumin [NDC 44206-310-90]
500 mL | 44206-310-50 | One single-dose vial containing 25 grams of albumin [NDC 44206-310-91]

STORAGE

ALBURX® 5, Albumin (Human) 5% solution should be stored at a temperature not exceeding 30°C (86°F). It should not be used after the expiration date printed on the label.

REFERENCES

1. Clowes GHA Jr, Vucinic M, Weidner MG. Ann. Surg. 1966;163:866.
2. Gaar KA Jr, Taylor AE, Owens LJ, Guyton AC. Amer. J. Physiol. 1967;213:79.
3. Heughan C, Niinikoski J, Hunt TK. Surg. Gynec. Obstet. 1972;135:257.
4. Hoye RC, Paulson DF, Ketcham AS. Surg. Gynec. Obstet. 1970;131:943.
5. Kinney JM, Egdahl RH, Zuidema GD. Manual of Preoperative and Postoperative Care, American College of Surgeons. Philadelphia: W. B. Saunders Co: 1971.
6. Lowenstein E. In: Sgouris JT, René A, ed. Proceedings of the Workshop on Albumin, February 12–13. Bethesda, Maryland 20014: DHEW Publication NIH 76-925, NHLI; p. 302, 1975.
7. Moss G. Surg. Forum. 1967;18:333.
8. Ring J, Messmer K. Lancet. 1977;1:466.
9. Ring J, Seifert J, Lob G, Coulin K, Brendel W. Klin. Wschr. 1974;52:595.
10. Sgouris JT, René A, ed. Proceedings of the Workshop on Albumin, February 12–13. Bethesda, Maryland 20014: DHEW Publication NIH 76-925, NHLI; 1975.
11. Simmons RL, Heisterkamp CA, Collins JA, Bredenberg CE, Martin AM. J. Trauma. 1969;9:760.
12. Skillman JJ, Parikh BM, Tanenbaum BJ. Amer. J. Surg. 1970;119:440.
13. Skillman JJ, Restall DS, Salzman EW. Surgery. 1975;78:291.
14. Skillman JJ, Tanenbaum BJ. Current Topics in Surgical Research. Vol. 2. New York: Academic Press; 1970:523.
15. Starling EH. J. Physiol. 1896;19:312-326.
16. Tullis JL. JAMA. 1977:237:355,460.

Manufactured by:
CSL Behring AG
Bern, Switzerland
US License No. 1766

Distributed by:
CSL Behring LLC
Kankakee, IL 60901 USA

Revised July 2022

Principal Display Panel - 250 mL Vial Carton

NDC 44206-310-25
5%

Albumin (Human)
5% Solution
AlbuRx® 5
250 mL

For intravenous
administration

Rx only

CSL Behring

PRINCIPAL DISPLAY PANEL - 500 mL Vial Carton

NDC 44206-310-50
5%

Albumin (Human)
5% Solution
AlbuRx® 5
500 mL

For intravenous
administration

Rx only

CSL Behring